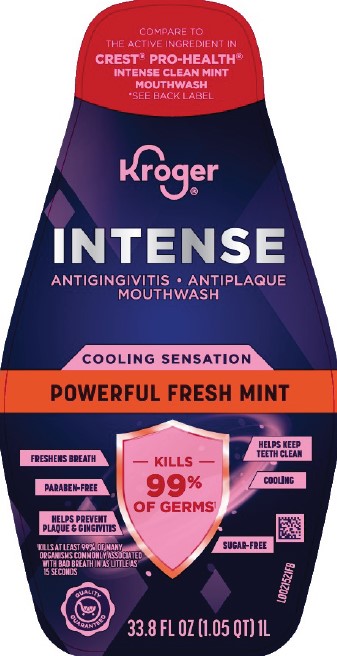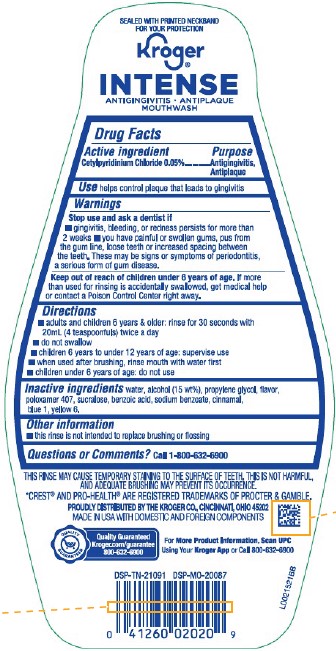 DRUG LABEL: Antigingivitis/Antiplaque
NDC: 59450-953 | Form: MOUTHWASH
Manufacturer: The Kroger Co.
Category: otc | Type: HUMAN OTC DRUG LABEL
Date: 20260227

ACTIVE INGREDIENTS: CETYLPYRIDINIUM CHLORIDE 0.5 mg/1 mL
INACTIVE INGREDIENTS: WATER; ALCOHOL; PROPYLENE GLYCOL; POLOXAMER 407; SUCRALOSE; BENZOIC ACID; SODIUM BENZOATE; CINNAMALDEHYDE; FD&C BLUE NO. 1; FD&C YELLOW NO. 6

Kroger D53.000/D53AA
Powerful Fresh Mint Mouthwash

Tamper Evident Statement

SEALED WITH PRINTED NECKBAND FOR YOUR PROTECTION

Claims

Kroger®

INTENSE

ANTIGINGIVITIS

ANTIPLAQUE

MOUTHWASH

Active Ingredient

Cetylpyridinium Chloride 0.05%

Purpose

Antigingivitis, Antiplaque

Use

helps control plaque that leads to gingivitis

Warnings

for this product

Stop use and ask a dentist if

- gingivitis, bleeding, or redness persists for more than 2 weeks
- you have painful or swollen gums, pus from the gum line, loose teeth or increased spacing between the teeth. These may be signs or symptoms of periodontitis, a serious form of gum disease.

Keep out of reach of children under 6 years of age.

If more than used for rinsing is accidentally swallowed, get medical help or contact a Poison Control Center right away.

Directions

- adults and children 6 years & older: rinse for 30 seconds with 20 mL (4 teaspoonfuls) twice a day
- do not swallow
- children 6 years to under 12 years of age: supervise use
- when used after brushing, rinse mouth with water first
- children under 6 years of age: do not use

Inactive ingredients

water, alcohol (15 wt%), propylene glycol, flavor, poloxamer 407, sucralose, benzoic acid, sodium benzoate, cinnamal, blue 1, yellow 6

Other information

- this rinse is not intended to replace brushing or flossing

Questions or Comments?

Call 1-800-632-6900

Disclaimers

This may cause temporary staining to the surface of teeth. This is not harmful, and adequate brushing may prevent its occurrence.

*CREST® AND PRO-HEALTH®ARE REGISTERED TRADEMARKS OF PROCTER & GAMBLE.

Adverse Reaction

PROUDLY DISTRIBUTED BY THE KROGER CO., CINCINNATI, OHIO 45202

MADE IN USA WITH DOMESTIC AND FOREIGN COMPONENTS

QUALITY GUARANTEED

Kroger.com/guarantee

800-632-6900

FOR MORE PRODUCT INFORMATION, SCAN UPC USING YOUR KROGER APP OR CALL 800-632-6900

DSP-TN-21091 DSP-MO-20087

Principal Panel Display

COMPARE TO the active ingredient in CREST® PRO-HEALTH® INTENSE CLEAN MINT MOUTHWASH

*See Back Label

Kroger®

INTENSE

ANTIGINGIVITIS/ANTIPLAQUE

MOUTHWASH

COOLING SENSATION

POWERFUL FRESH MINT

KILLS 99% OF GERMS†

FRESHENS BREATH

HELPS KEEP TEETH CLEAN

PARABEN-FREE

COOLING

HELPS PREVENT PLAQUE & GINGIVITIS

SUGAR FREE

†Kills at least 99% of many organisms commonly assoicated with bad breath in as little as 15 seconds

QUALITY GUARANTEED

33.8 FL OZ (1.5 QT) 1 L